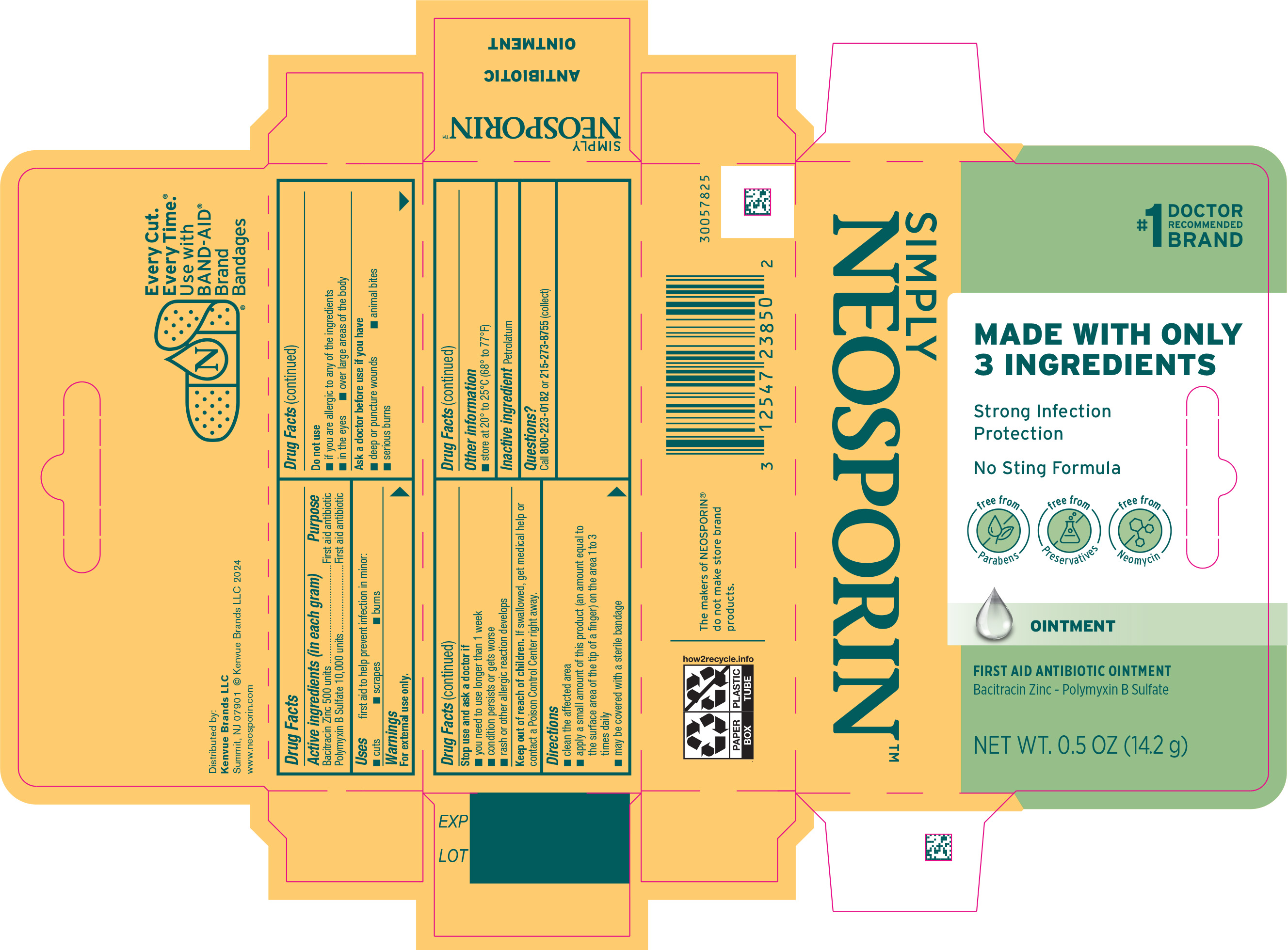 DRUG LABEL: Simply Neosporin
NDC: 69968-0612 | Form: OINTMENT
Manufacturer: Kenvue Brands LLC
Category: otc | Type: HUMAN OTC DRUG LABEL
Date: 20241113

ACTIVE INGREDIENTS: BACITRACIN ZINC 500 [iU]/1 g; POLYMYXIN B SULFATE 10000 [iU]/1 g
INACTIVE INGREDIENTS: PETROLATUM

SIMPLY NEOSPORIN™

Drug Facts

ACTIVE INGREDIENT

Active ingredient (in each gram) | Purpose
Bacitracin Zinc 500 units | First aid antibiotic
Polymyxin B Sulfate 10,000 units | First aid antibiotic

Warnings

For external use only.

Do not use

- if you are allergic to any of the ingredients
- in the eyes
- over large areas of the body

Ask a doctor before use if you have

- deep or puncture wounds
- animal bites
- serious burns

Stop use and ask a doctor if

- you need to use longer than 1 week
- condition persists or gets worse
- rash or other allergic reaction develops

Keep out of reach of children. If swallowed, get medical help or contact a Poison Control Center right away.

Uses

first aid to help prevent infection in minor:

- cuts
- scrapes
- burns

Directions

- clean the affected area
- apply a small amount of this product (an amount equals to the surface area of the tip of a finger) on the area 1 to 3 times daily
- may be covered with a sterile bandage

Other information

- store at 20° to 25° C (68° - 77° F)

Inactive ingredients

Petrolatum

Questions?

Call 800-223-0182 or 215-273-8755 (collect)

Distributed by:

Kenvue Brands LLC
Summit, NJ 07901

PRINCIPAL DISPLAY PANEL - 14.2 g Tube Carton

#1 DOCTOR
RECOMMENDED
BRAND

SIMPLY

NEOSPORIN™

MADE WITH ONLY

3 INGREDIENTS

Strong Infection
Protection

No Sting Formula

free from
Parabens

free from
Preservatives

free from
Neomycin

OINTMENT

FIRST AID ANTIBIOTIC OINTMENT

Bacitracin Zinc - Polymyxin B Sulfate

NET WT. 0.5 OZ (14.2 g)